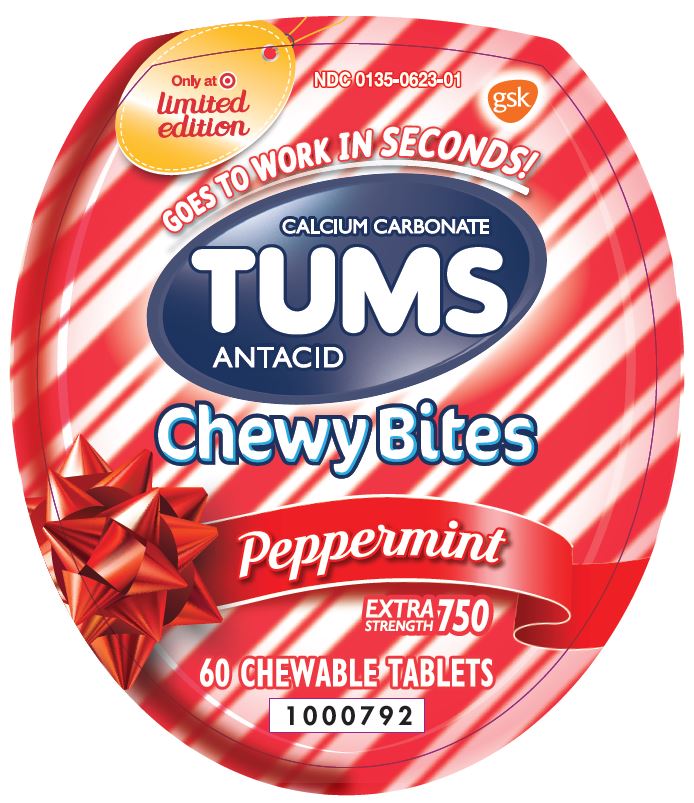 DRUG LABEL: Tums
NDC: 0135-0623 | Form: TABLET, CHEWABLE
Manufacturer: Haleon US Holdings LLC
Category: otc | Type: HUMAN OTC DRUG LABEL
Date: 20240503

ACTIVE INGREDIENTS: CALCIUM CARBONATE 750 mg/1 1
INACTIVE INGREDIENTS: ACACIA; AMMONIA; YELLOW WAX; CARNAUBA WAX; CITRIC ACID MONOHYDRATE; COCONUT OIL; STARCH, CORN; CORN SYRUP; ICODEXTRIN; ETHYL ACETATE; FD&C BLUE NO. 1; ALUMINUM OXIDE; FD&C RED NO. 40; FD&C YELLOW NO. 5; ISOPROPYL ALCOHOL; MALTODEXTRIN; BUTYL ALCOHOL; PHOSPHORIC ACID; PROPYLENE GLYCOL; WATER; SHELLAC; SODIUM BENZOATE; SORBIC ACID; SORBITOL; SOYBEAN OIL; LECITHIN, SOYBEAN; SUCROSE; TERT-BUTYLHYDROQUINONE; TITANIUM DIOXIDE

Drug Facts

Active ingredient (per tablet)

Calcium carbonate 750 mg

Purpose

Antacid

Uses

relieves

- heartburn
- acid indigestion
- sour stomach
- upset stomach associated with these symptoms

Warnings

Ask a doctor or pharmacist before use if you are

presently taking a prescription drug. Antacids may interact with certain prescription drugs.

When using this product

- do not take more than 6 tablets in 24 hours
- if pregnant do not take more than 6 tablets in 24 hours
- do not use the maximum dosage for more than 2 weeks, except under the advice and supervision of a doctor

Directions

- adults and children 12 years of age and over: chew 2-4 tablets as symptoms occur, or as directed by a doctor. Chew or crush tablets completely before swallowing.
- do not take for symptoms that persist for more than 2 weeks unless advised by a doctor

Other information

- each chewable tablet contains: elemental calcium 300 mg
- do not store above 25°C (77°F)

Inactive ingredients

acacia gum, ammonium hydroxide, beeswax, carnauba wax, citric acid, coconut oil, corn starch, corn syrup, dextrin, ethanol, ethyl acetate, FD&C blue #1 alum lake, FD&C red #40, FD&C red #40 alum lake, FD&C yellow #5 alum lake (tartrazine), FD&C yellow #6 alum lake, flavors, gum arabic, isopropyl alcohol, maltodextrin, n-butyl alcohol, phosphoric acid, propylene glycol, purified water, shellac, sodium benzoate, sorbic acid, sorbitol, soybean oil, soy lecithin, sucrose, TBHQ, titanium dioxide, vegetable oil

Questions or comments?

1-800-897-7535

Additional Information

Safety sealed – Do not use if printed inner seal beneath cap is missing or broken.

Distributed by:

GSK Consumer Healthcare
Warren, NJ 07059
Trademarks are owned by or licensed
to the GSK group of companies.
©2020 GSK group of companies or its licensor.

1000793

Package/Label Principal Display Panel

Only at Target
limited edition

NDC 0135-0623-01

GOES TO WORK IN SECONDS!

CALCIUM CARBONATE

TUMS

ANTACID

Chewy Bites

Peppermint

EXTRA STRENGTH 750

60 CHEWABLE TABLETS

1000792